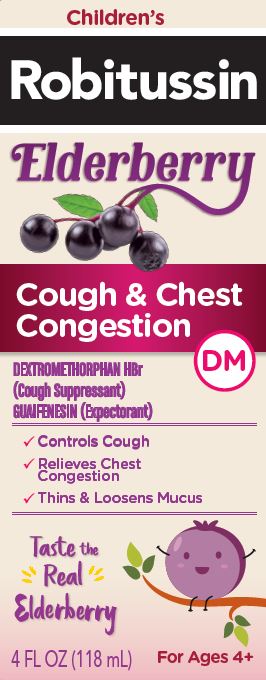 DRUG LABEL: Childrens Robitussin Elderberry Cough and Chest Congestion DM
NDC: 0031-2098 | Form: SOLUTION
Manufacturer: Haleon US Holdings LLC
Category: otc | Type: HUMAN OTC DRUG LABEL
Date: 20251125

ACTIVE INGREDIENTS: DEXTROMETHORPHAN HYDROBROMIDE 20 mg/20 mL; GUAIFENESIN 400 mg/20 mL
INACTIVE INGREDIENTS: ANHYDROUS CITRIC ACID; CARBOXYMETHYLCELLULOSE SODIUM, UNSPECIFIED; GLYCERIN; POLYETHYLENE GLYCOL, UNSPECIFIED; PROPYLENE GLYCOL; WATER; SODIUM BENZOATE; SODIUM CITRATE, UNSPECIFIED FORM; SODIUM GLUCONATE; SUCRALOSE; XANTHAN GUM; ZINC GLUCONATE

Drug Facts

Active ingredients (in each 20 mL)

Dextromethorphan HBr 20 mg

Guaifenesin 400 mg

Purposes

Cough suppressant

Expectorant

Uses

- temporarily relieves cough due to minor throat and bronchial irritation as may occur with a cold
- helps loosen phlegm (mucus) and thin bronchial secretions to drain bronchial tubes

Warnings

DO NOT USE

Do not useif you are now taking a prescription monoamine oxidase inhibitor (MAOI) (certain drugs for depression, psychiatric, or emotional conditions, or Parkinson's disease), or for 2 weeks after stopping the MAOI drug. If you do not know if your prescription drug contains an MAOI, ask a doctor or pharmacist before taking this product.

Ask a doctor before use if you have

- cough that occurs with too much phlegm (mucus)
- cough that lasts or is chronic such as occurs with smoking, asthma, chronic bronchitis, or emphysema.

Stop use and ask a doctor ifcough lasts more than 7 days, comes back, or is accompanied by fever, rash, or persistent headache.
These could be signs of a serious condition.

PREGNANCY OR BREAST FEEDING

If pregnant or breast-feeding,ask a health professional before use.

Keep out of reach of children.In case of overdose, get medical help or contact a Poison Control Center right away.

Directions

- do not take more than 6 doses in any 24-hour period
- measure only with dosing cup provided
- keep dosing cup with product
- mL = milliliter

age | dose
children under 4 years | do not use
children 4 to under 6 years | 5 mL every 4 hours
children 6 to under 12 years | 10 mL every 4 hours
adults and children; 12 years and over | 20 mL every 4 hours

Other information

- each 20 mL contains:potassium 5 mg, sodium 21 mg
- store at 20-25°C (68-77°F). Do not refrigerate.

Inactive ingredients

anhydrous citric acid, black elderberry juice concentrate (for flavor), carboxymethylcellulose sodium, glycerin, liquid glucose, maltodextrin, natural and artificial flavors, polyethylene glycol, propylene glycol, purified water, sodium benzoate, sodium citrate, sodium gluconate, sucralose, xanthan gum, zinc gluconate

Questions or comments?

call weekdays from 8 AM to 6 PM EST at 1-800-245-1040

Additional information

PARENTS:

Learn about teen medicine abuse

www.StopMedicineAbuse.org

Packaged with Tamper-Evident bottle cap.

Do Not Use if breakable ring is separated or missing.

PRINCIPAL DISPLAY PANEL

Children’s

Robitussin

Elderberry

Cough & Chest
Congestion DM

DEXTROMETHORPHAN HBr (Cough Suppressant)
GUAIFENESIN (Expectorant)

- Controls Cough
- Relieves Chest Congestion
- Thins & Loosens Mucus

Taste the
Real Elderberry

4 FL OZ (118 mL)

For Ages 4+